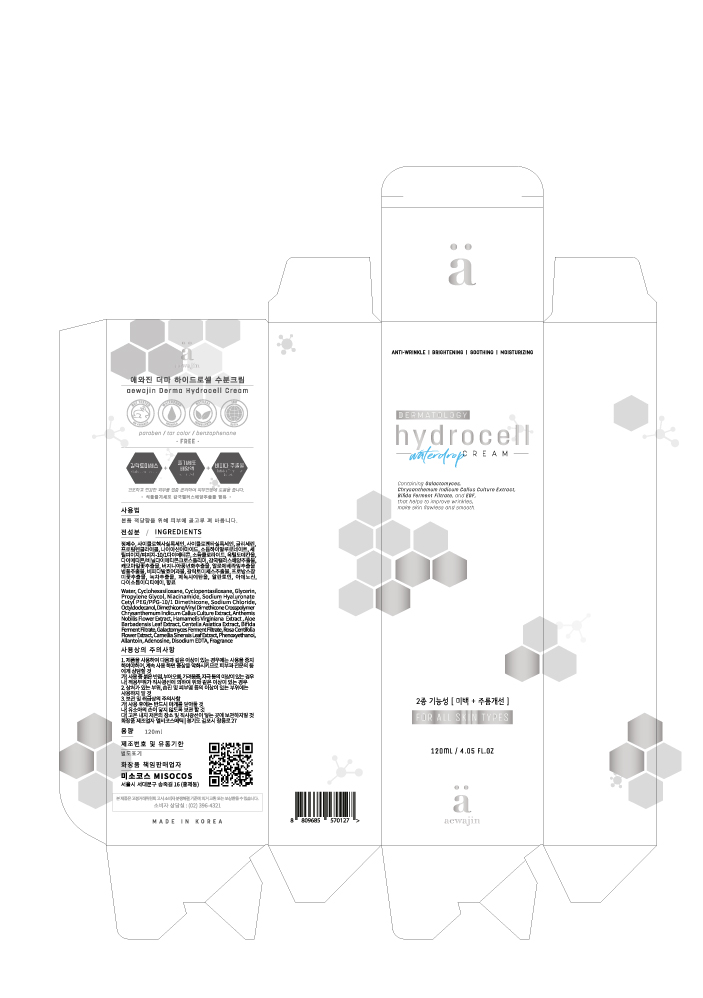 DRUG LABEL: aewajin Derma Hydrocell
NDC: 73466-0004 | Form: CREAM
Manufacturer: MISOCOS
Category: otc | Type: HUMAN OTC DRUG LABEL
Date: 20240705

ACTIVE INGREDIENTS: GLYCERIN 5 g/100 mL
INACTIVE INGREDIENTS: WATER; ALLANTOIN

Drug Facts

ACTIVE INGREDIENT

glycerin

INACTIVE INGREDIENT

propylene glycol, niacinamide, allantoin, adenosine, disodium EDTD, etc.

PURPOSE

whitening, wrinkle care

keep out of reach of the children

INDICATIONS AND USAGE

take a suitable amount on the skin

WARNINGS

■ if following abnormal symptoms occurs after use , stop use and consult with a skin specialist

red specks, swelling, itching

■ don’t use on the part where there is injury, eczema, or dermatitis

Keep out of reach of children

■ if swallowed, get medical help or contact a person control center immediately

DOSAGE AND ADMINISTRATION

for external use only